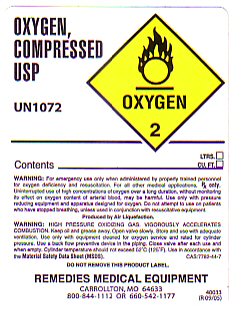 DRUG LABEL: OXYGEN
NDC: 67378-001 | Form: GAS
Manufacturer: B-Pharm, Inc dba Remedies Medical Equipment
Category: prescription | Type: HUMAN PRESCRIPTION DRUG LABEL
Date: 20100101

ACTIVE INGREDIENTS: OXYGEN 99 L/100 L

OXYGEN COMPRESSED LABEL

OXYGEN COMPRESSED USP

UN 1072

CONTENTS _________________________ LTRS _____ CU. FT. _______

REMEDIES MEDICAL EQUIPMENT

CARROLLTON, MO 64633

800-844-1112 OR 660-542-1177

40033 (R 09/05)

WARNINGS AND PRECAUTIONS

OXYGEN COMPRESSED USP

UN1072 OXYGEN 2

WARNING: For emergency use only when administered by properly trained personnel for Oxygen deficiency and resuscitation. For all other medical applications Rx Only. Uninterrupted use of high concentrations of Oxygen over a long duration, without monitoring its effect on oxyen content of arterial blood may be harmful. Use only with pressure reducing equipment and apparatus designed for Oxygen. Do not attempt to use on patients who have stopped breathing, unless used in conjunction with resuscitative equipment. PRODUCED BY AIR LIQUEFACTION.

Warning: HIGH PRESSURE OXIDIZING GAS. VIGOROUSLY ACCELERATED COMBUSTION. Keep oil and grease away. Open valve slowly. Store and use with adequate ventilation. Use only with equipment cleaned for Oxygen Service and rated for cylinder pressure. Use a back flow preventative device in piping. Close valve after each use and when empty. Cylinder temperature should not exceed 52 C (125 F) Use in accordance with the Material Safety Data Sheet (MSDS) CAS 7782-44-7 Do Not Remove this Product Label